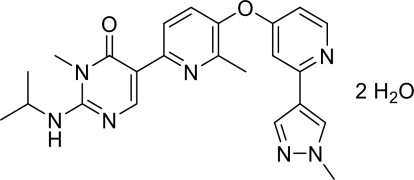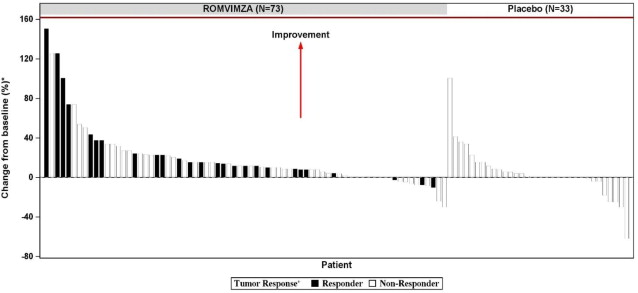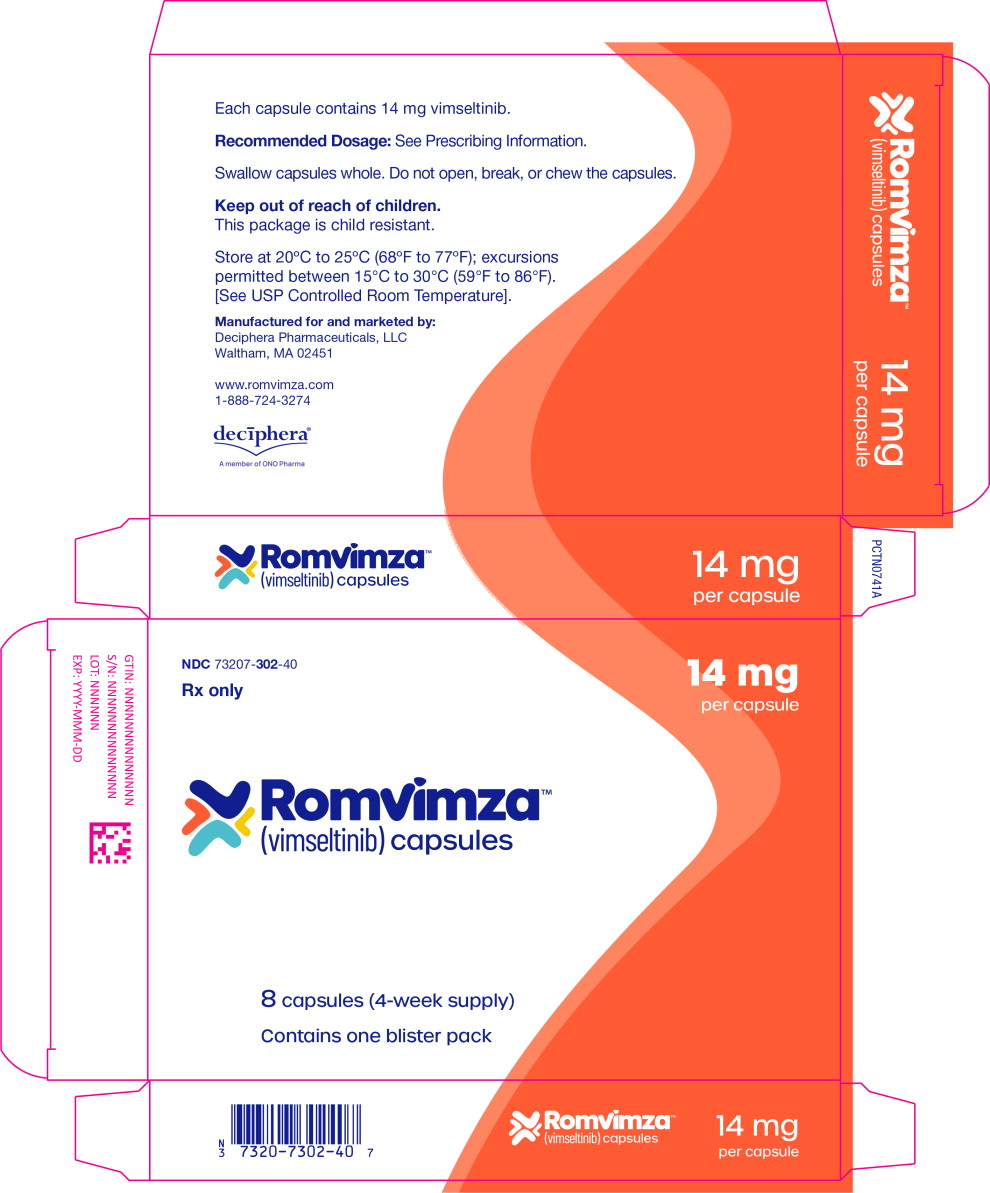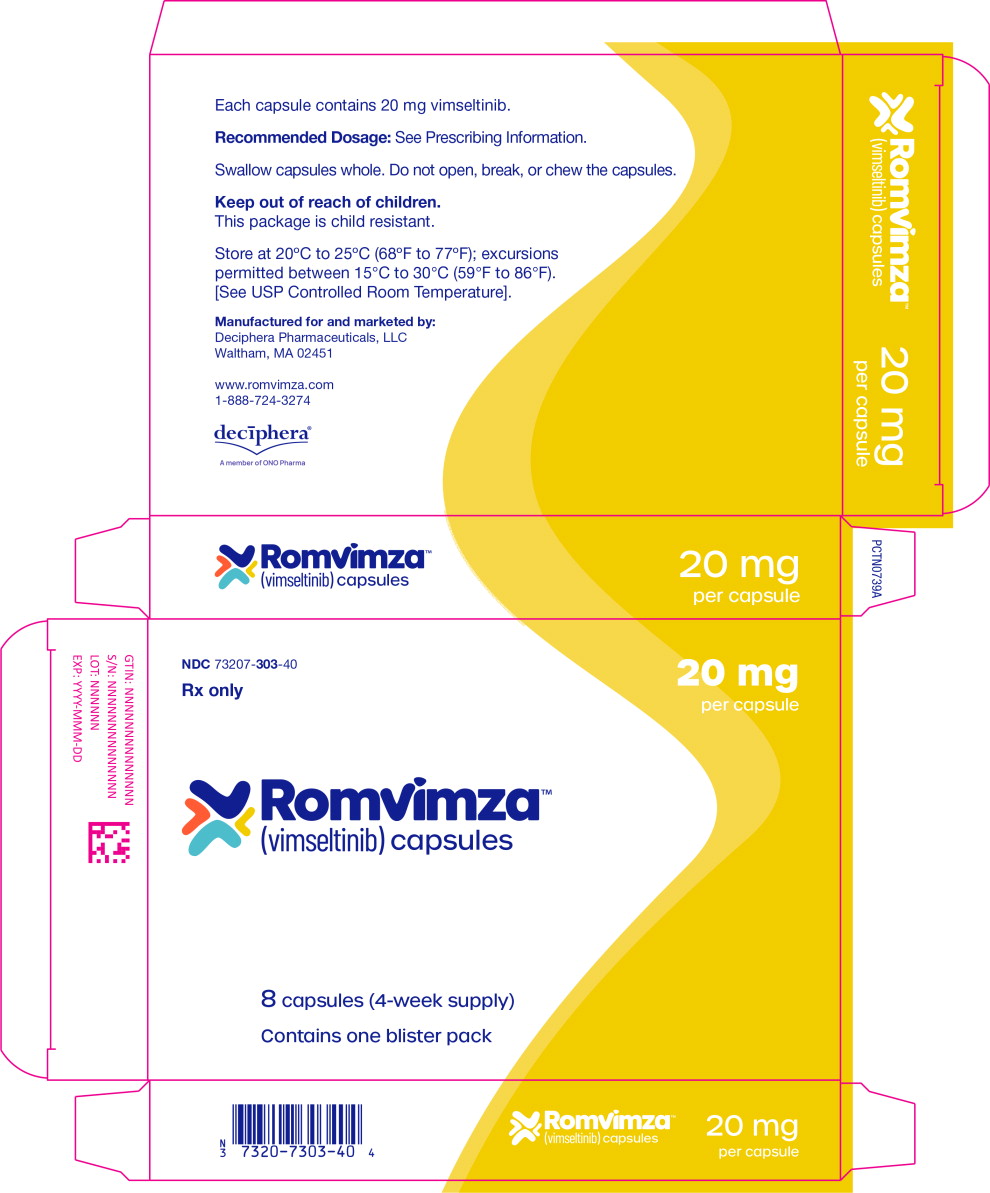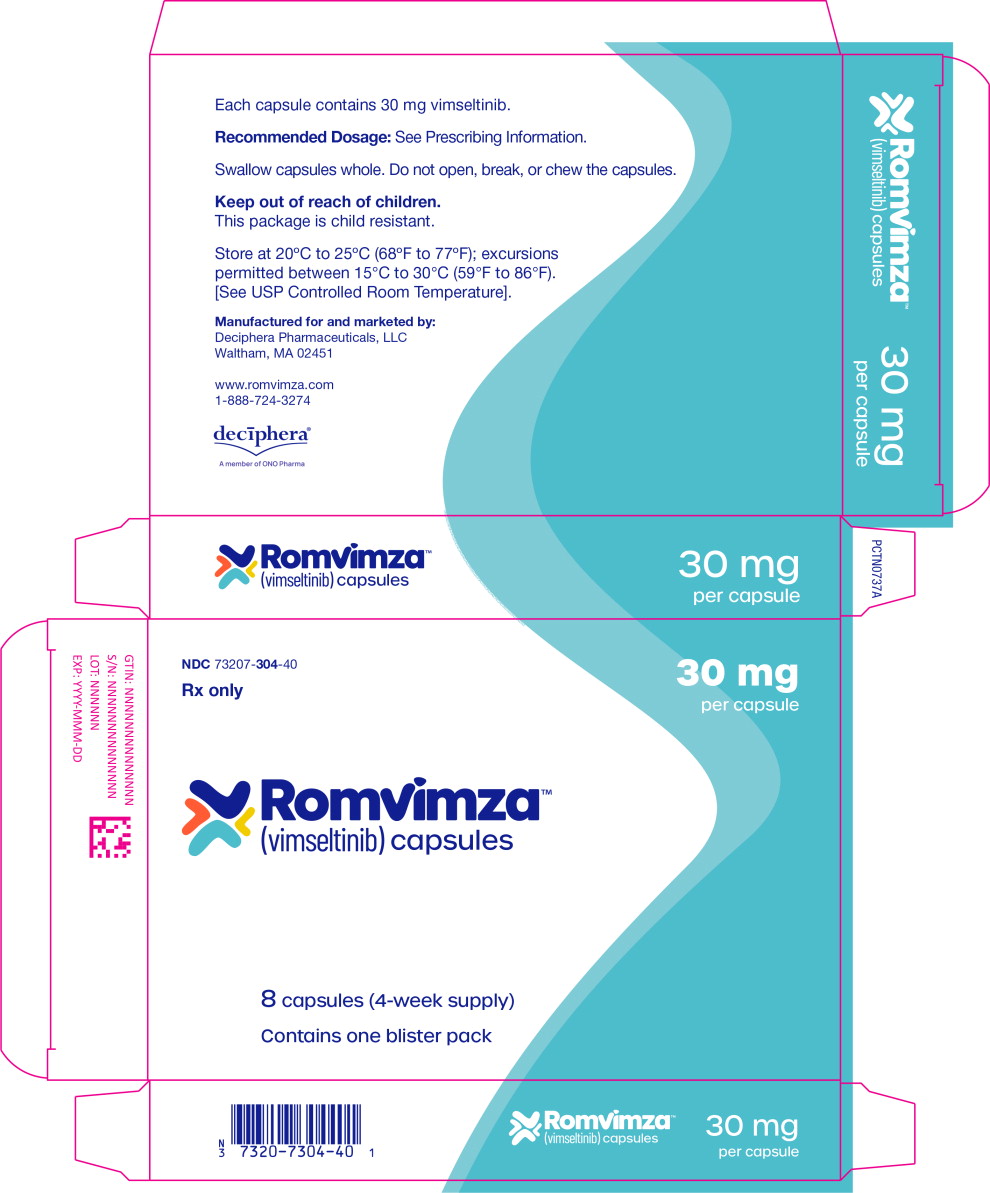 DRUG LABEL: ROMVIMZA
NDC: 73207-302 | Form: CAPSULE
Manufacturer: Deciphera Pharmaceuticals, LLC
Category: prescription | Type: HUMAN PRESCRIPTION DRUG LABEL
Date: 20251222

ACTIVE INGREDIENTS: Vimseltinib 14 mg/1 1
INACTIVE INGREDIENTS: Lactose monohydrate; Crospovidone; Magnesium stearate

HIGHLIGHTS OF PRESCRIBING INFORMATION

These highlights do not include all the information needed to use ROMVIMZATM safely and effectively. See full prescribing information for ROMVIMZATM.
ROMVIMZATM (vimseltinib) capsules, for oral use
Initial U.S. Approval: 2025

1 INDICATIONS AND USAGE

ROMVIMZA is a kinase inhibitor indicated for treatment of adult patients with symptomatic tenosynovial giant cell tumor (TGCT) for which surgical resection will potentially cause worsening functional limitation or severe morbidity. (1)

2 DOSAGE AND ADMINISTRATION

- Recommended Dosage: 30 mg orally twice weekly, with a minimum of 72 hours between doses as described in the blister package. (2.1)
- See full prescribing information for dosage modifications due to hepatotoxicity and drug interactions. (2.2, 2.3)

3 DOSAGE FORMS AND STRENGTHS

Capsules: 14 mg, 20 mg, 30 mg. (3)

4 CONTRAINDICATIONS

None (4)

5 WARNINGS AND PRECAUTIONS

Hepatotoxicity: Elevated AST and ALT can occur. Evaluate liver tests prior to initiation of treatment and during treatment. (2.2, 5.1)

Embryo-fetal toxicity: Can cause fetal harm. Advise patients of reproductive potential of the potential risk to a fetus and to use effective contraception. (5.2, 8.1, 8.3)

Allergic Reactions to FD&C Yellow No. 5 (tartrazine) and No. 6 (Sunset Yellow FCF): 14 mg capsule contains FD&C Yellow No. 6 (Sunset Yellow FCF); 20 mg capsule contains FD&C Yellow No.5 (tartrazine) and No. 6 (Sunset Yellow FCF) as color additives, which may cause allergic reactions (including bronchial asthma) in certain susceptible patients. (5.3)

Increased serum creatinine without affecting renal function: Increases in serum creatinine can occur. Use alternative measures that are not based on serum creatinine to assess renal function. (5.4)

6 ADVERSE REACTIONS

Most common adverse reactions (incidence ≥20%), including laboratory abnormalities are increased AST, periorbital edema, fatigue, rash, increased cholesterol, peripheral edema, face edema, decreased neutrophils, decreased leukocytes, pruritus, and increased ALT. (6.1)

To report SUSPECTED ADVERSE REACTIONS, contact Deciphera Pharmaceuticals, LLC at 1-888-724-3274 or FDA at 1-800-FDA-1088 or www.fda.gov/medwatch.

7 DRUG INTERACTIONS

- P-glycoprotein (P-gp) substrates: Avoid concomitant use of ROMVIMZA with P-gp substrates. If concomitant use cannot be avoided, take ROMVIMZA at least 4 hours prior to P-gp substrates. Concomitant use of vimseltinib with P-gp substrates may increase exposure of these substrates. (2.3, 7.1)
- Breast Cancer Resistance Protein (BCRP) substrates: Avoid concomitant use of ROMVIMZA with BCRP substrates. Concomitant use of vimseltinib with BCRP substrates may increase exposure of these substrates. (7.1)
- Organic Cation Transporter 2 (OCT) substrates: Avoid concomitant use of ROMVIMZA with OCT2 substrates. Concomitant use of vimseltinib with OCT2 substrates may increase exposure of these substrates. (7.1)

8 USE IN SPECIFIC POPULATIONS

Lactation: Advise not to breastfeed. (8.2)

FULL PRESCRIBING INFORMATION

1 INDICATIONS AND USAGE

ROMVIMZA is indicated for treatment of adult patients with symptomatic tenosynovial giant cell tumor (TGCT) for which surgical resection will potentially cause worsening functional limitation or severe morbidity.

2 DOSAGE AND ADMINISTRATION

2.1 Recommended Dosage

The recommended dosage of ROMVIMZA is 30 mg orally taken twice weekly, with a minimum of 72 hours between doses, as directed on the blister package [see Clinical Pharmacology (12.3)]. Instruct patients to follow the schedule on the blister package and to take ROMVIMZA on the same days each week.

- ROMVIMZA may be taken with or without food.
- Swallow ROMVIMZA capsules whole. Do not open, break, or chew the capsules.
- If a dose is missed by 48 hours or less, take the missed dose as soon as possible and take the next dose on its regularly scheduled day. If a dose is missed by more than 48 hours, skip the missed dose, and take the next dose on its regularly scheduled day.
- If vomiting occurs within 30 minutes of taking a dose, repeat that dose. Otherwise, take the next dose on its regularly scheduled day.

2.2 Dose Modifications for Adverse Reactions

The recommended dose reductions for adverse reactions are provided in Table 1.

Table 1: Recommended Dose Reductions
Dose Reduction | Twice Weekly Dose
First | 20 mg
Second | 14 mg

Permanently discontinue ROMVIMZA in patients who are unable to tolerate 14 mg orally twice weekly.

The recommended dosage modifications for hepatotoxicity are summarized in Table 2.

Table 2: Recommended Dosage Modifications for Hepatotoxicity
Hepatotoxicity Severity | ROMVIMZA Dosage Modifications
AST and/or ALT increases >3–5 times ULN and total bilirubin increases up to 2 times ULN | Withhold ROMVIMZA until AST and ALT resolve to baseline or ≤3 times ULN, and bilirubin resolves to baseline. Resume at the next lower dose level once Hy's law has been definitively ruled out. Permanently discontinue if adverse reaction does not resolve within 4 weeks.
OR | Withhold ROMVIMZA until AST and ALT resolve to baseline or ≤3 times ULN, and bilirubin resolves to baseline. Resume at the next lower dose level once Hy's law has been definitively ruled out. Permanently discontinue if adverse reaction does not resolve within 4 weeks.
Total bilirubin increases up to 2 times ULN | Withhold ROMVIMZA until AST and ALT resolve to baseline or ≤3 times ULN, and bilirubin resolves to baseline. Resume at the next lower dose level once Hy's law has been definitively ruled out. Permanently discontinue if adverse reaction does not resolve within 4 weeks.
AST and/or ALT increases >3–5 times ULN, and total bilirubin increases >2 times ULN or INR >1.5 and ALP <2 times ULN | Withhold ROMVIMZA until AST and ALT resolve to baseline or ≤3 times ULN, and bilirubin resolves to baseline. Resume at the next lower dose level once Hy's law has been definitively ruled out. Permanently discontinue if adverse reaction does not resolve within 4 weeks.
OR | Withhold ROMVIMZA until AST and ALT resolve to baseline or ≤3 times ULN, and bilirubin resolves to baseline. Resume at the next lower dose level once Hy's law has been definitively ruled out. Permanently discontinue if adverse reaction does not resolve within 4 weeks.
Total bilirubin increases >2 times ULN | Withhold ROMVIMZA until AST and ALT resolve to baseline or ≤3 times ULN, and bilirubin resolves to baseline. Resume at the next lower dose level once Hy's law has been definitively ruled out. Permanently discontinue if adverse reaction does not resolve within 4 weeks.
AST and/or ALT increases >5–8 times ULN, and total bilirubin ≤ULN and without clinical symptoms | Withhold ROMVIMZA until AST and ALT resolve to ≤3 times ULN or baseline. Permanently discontinue if adverse reaction does not resolve within 4 weeks.
AST and/or ALT increases >5-8 times ULN and total bilirubin increase >ULN, or INR >1.5, or ALP >2 times ULN | Permanently discontinue ROMVIMZA.
AST and/or ALT increases >8 times ULN | Permanently discontinue ROMVIMZA.
ALT = alanine aminotransferase; ALP = alkaline phosphatase; AST = aspartate aminotransferase; INR = International normalized ratio; ULN = upper limit of normal

2.3 Dosage Modification for P-glycoprotein (P-gp) Substrates

Avoid concomitant use of ROMVIMZA with P-gp substrates. If concomitant use of a P-gp substrate is unavoidable, administer ROMVIMZA at least 4 hours before taking the P-gp substrate unless otherwise recommended in the substrate Prescribing Information [see Drug Interactions (7.1)].

3 DOSAGE FORMS AND STRENGTHS

14 mg capsule

Orange cap, white body size 4 capsule imprinted with “DCV14” in black ink.

20 mg capsule

Yellow cap, white body size 2 capsule imprinted with “DCV20” in black ink.

30 mg capsule

Light blue cap, white body size 1 capsule imprinted with “DCV30” in black ink.

4 CONTRAINDICATIONS

None.

5 WARNINGS AND PRECAUTIONS

5.1 Hepatotoxicity

Cases of serious and fatal liver injury have occurred with the use of another kinase inhibitor that targets CSF1R [see Clinical Pharmacology (12.1)]. Serious and fatal liver injury have not been observed with ROMVIMZA.

Across clinical trials in 253 patients treated with ROMVIMZA, 2% had Grade 3 increased AST, and 1% had Grade 3 increased ALT. Dose interruptions occurred in 2% of patients and dose reductions occurred in 1% of patients due to AST/ALT increase. One patient discontinued therapy due to Grade 3 AST increased.

Avoid ROMVIMZA in patients with pre-existing increased serum transaminases; total bilirubin or direct bilirubin (>ULN); or active liver or biliary tract disease, including ALP. Monitor liver tests, including AST, ALT, total bilirubin, direct bilirubin, ALP and gamma-glutamyl transferase (GGT), prior to initiation of ROMVIMZA, twice a month for the first two months and once every 3 months for the first year of therapy and as clinically indicated thereafter. Withhold and reduce the dose, or permanently discontinue ROMVIMZA based on the severity of the hepatotoxicity [see Dosage and Administration (2.2)].

5.2 Embryo-Fetal Toxicity

Based on data from animal studies and its mechanism of action, ROMVIMZA can cause fetal harm when administered to pregnant women. In female rats administered vimseltinib, fetal structural abnormalities occurred at exposures that were at least 3 times the recommended dose based on area under the curve (AUC). Advise pregnant women on the potential risk to the fetus.

Advise females of reproductive potential and males with female partners of reproductive potential to use effective contraception during treatment with ROMVIMZA and for 1 month after the last dose [see Use in Specific Populations (8.1, 8.3)].

5.3 Allergic Reactions to FD&C Yellow No.5 (Tartrazine) and No. 6 (Sunset Yellow FCF)

ROMVIMZA 20 mg capsule contains FD&C Yellow No. 5 (tartrazine) which may cause allergic reactions (including bronchial asthma) in certain susceptible patients. Although the overall incidence of FD&C Yellow No. 5 (tartrazine) sensitivity in the general population is low, it is frequently seen in patients who also have aspirin sensitivity.

ROMVIMZA 14 mg and 20 mg capsules contain FD&C Yellow No.6 (Sunset Yellow FCF), which may cause allergic reactions.

5.4 Increased Creatinine without Affecting Renal Function

In MOTION, serum creatinine increased (mean increase of 19 μmol/L) and reached a maximum mean increase by 10.4 weeks compared to baseline. These increases in serum creatinine may not be associated with changes in renal function. Increases in creatinine reversed upon ROMVIMZA discontinuation. The increases in serum creatinine may be due to inhibition of renal tubular secretion transporters [see Drug Interactions (7.1) and Clinical Pharmacology (12.3)]. During ROMVIMZA treatment, use alternative measures that are not based on serum creatinine to assess renal function.

6 ADVERSE REACTIONS

The following clinically significant adverse reactions are described elsewhere in the labeling:

- Hepatotoxicity [see Warnings and Precautions (5.1)]

6.1 Clinical Trials Experience

Because clinical trials are conducted under widely varying conditions, adverse reaction rates observed in the clinical trials of a drug cannot be directly compared to rates in the clinical trials of another drug and may not reflect the rates observed in practice.

The pooled safety population described in the Warnings and Precautions reflects exposure to ROMVIMZA in 83 patients with TGCT enrolled in the double-blind portion and in 35 patients with TGCT in the open-label portion who crossed over to ROMVIMZA in MOTION, and in 135 patients with TGCT or solid tumors in other clinical trials.

The safety of ROMVIMZA was evaluated in 83 adult patients with TGCT in MOTION [see Clinical Studies (14)]. MOTION excluded patients with bilirubin, AST, or ALT >ULN. All patients received ROMVIMZA twice weekly until disease progression or unacceptable toxicity. Among these patients, 82% were exposed for 6 months or longer and 30% were exposed for greater than one year.

Serious adverse reactions occurred in 2.4% of patients who received ROMVIMZA. Serious adverse reactions in ≥1% included subcutaneous abscess (1.2%) and cellulitis (1.2%).

Permanent discontinuation due to an adverse reaction occurred in 4.8% of patients who received ROMVIMZA. Adverse reactions leading to permanent discontinuation in one patient each included periorbital edema, neuropathy, rash, and hypertension.

Dose reductions due to an adverse reaction or laboratory abnormality occurred in 39% of patients who received ROMVIMZA. Adverse reactions leading to dose reductions in ≥2% of patients receiving ROMVIMZA were rash, periorbital edema, peripheral edema, fatigue, pruritus, face edema, increased CPK, neuropathy, and hypertension.

Dose interruptions due to an adverse reaction or laboratory abnormality occurred in 40% of patients who received ROMVIMZA. Adverse reactions leading to interruptions in ≥2% of patients included rash, fatigue, peripheral edema, increased CPK, periorbital edema, face edema, pruritus, neuropathy, and hypertension.

The most common (≥20%) adverse reactions, including laboratory abnormalities that occurred in patients receiving ROMVIMZA were increased AST, periorbital edema, fatigue, rash, increased cholesterol, peripheral edema, face edema, decreased neutrophils, decreased leukocytes, pruritus, and increased ALT. Table 3 and Table 4 summarize the adverse reactions and laboratory abnormalities in MOTION during the randomized phase through Week 25.

Table 3: Adverse Reactions Occurring in ≥10% of Patients Receiving ROMVIMZA with a Difference Between Arms of >5% Compared to Placebo Through Week 25 in MOTION
Adverse Reaction* | ROMVIMZA N=83 |  | Placebo N=39
Adverse Reaction* | All Grades (%) | Grade 3 or 4 (%) | All Grades (%) | Grade 3 or 4 (%)
Eye disorders
Periorbital edema^1 | 60 | 3.6 | 21 | 0
Lacrimation increased | 12 | 0 | 0 | 0
Dry eye^1 | 10 | 0 | 0 | 0
General disorders and administration site conditions
Fatigue^1 | 59 | 1.2 | 38 | 2.6
Peripheral edema^1 | 33 | 1.2 | 8 | 0
Face edema | 31 | 1.2 | 8 | 0
Skin and subcutaneous tissue disorders
Rash^1 | 47 | 3.6 | 5 | 0
Pruritus | 29 | 2.4 | 8 | 0
Vascular disorders
Hypertension | 17 | 4.8 | 10 | 2.6
Nervous system disorders
Neuropathy^1 | 12 | 1.2 | 2.6 | 0
*The severity of adverse reactions was assessed using CTCAE v5.0.
^1 Includes multiple related terms

Other clinically significant adverse reactions occurring in <10% of patients treated with ROMVIMZA include blurred vision (6%).

Table 4: Laboratory Abnormalities Worsening from Baseline in ≥10% of Patients Receiving ROMVIMZA with a Difference Between Arms of >5% Compared to Placebo Through Week 25 in MOTION
Laboratory Abnormalitya | ROMVIMZA N=83 |  | Placebo N=39 b
Laboratory Abnormalitya | All Grades (%) | Grade 3 or 4 (%) | All Grades (%) | Grade 3 or 4 (%)
Chemistry
AST increased | 92 | 0 | 11 | 0
Cholesterol increased | 43 | 0 | 16 | 0
ALT increased | 24 | 0 | 16 | 0
Creatinine increased | 17 | 0 | 2.6 | 0
ALP increased | 14 | 0 | 8 | 0
Magnesium increased | 13 | 1.2 | 2.6 | 0
Calcium decreased | 13 | 0 | 2.6 | 0
Hematology
Neutrophils decreased | 31 | 1.2 | 2.6 | 0
Leukocytes decreased | 29 | 0 | 8 | 0
AST – aspartate aminotransferase, ALT – alanine aminotransferase, ALP – alkaline phosphatase
a The severity of adverse reactions was assessed using CTCAE v5.0.
b The denominator used to calculate the rate was 83 for ROMVIMZA and 38 for placebo based on the number of patients with a baseline value and at least one post-treatment value.

Additional clinically significant laboratory abnormality: Increased Creatine Phosphokinase (CPK)

7 DRUG INTERACTIONS

7.1 Effects of ROMVIMZA on Other Drugs

Table 5 describes drug interactions where concomitant use with ROMVIMZA affects another drug.

Table 5: Effect of ROMVIMZA on Other Drugs
P-glycoprotein (P-gp) substrates
Prevention or Management | Avoid concomitant use with P-gp substrates while taking ROMVIMZA. If concomitant use cannot be avoided, take ROMVIMZA at least 4 hours prior to P-gp substrates [see Dosage and Administration (2.3)] unless otherwise recommended in the substrate Prescribing Information.
Mechanism and Clinical Effect(s) | This recommendation is based upon a mechanistic understanding of vimseltinib pharmacokinetics and it being a P-gp inhibitor in vitro [see Clinical Pharmacology (12.3)]. Concomitant use of ROMVIMZA with P-gp substrates may increase exposure of these substrates; however, this has not been studied clinically.
Breast Cancer Resistance Protein (BCRP) substrates
Prevention or Management | Avoid concomitant use with BCRP substrates while taking ROMVIMZA. Refer to the Prescribing Information of the BCRP substrate for dose modifications if concomitant use cannot be avoided.
Mechanism and Clinical Effect(s) | This recommendation is based upon a mechanistic understanding of vimseltinib pharmacokinetics and it being a BCRP inhibitor in vitro [see Clinical Pharmacology (12.3)]. Concomitant use of ROMVIMZA with BCRP substrates may increase exposure of these substrates; however, this has not been studied clinically.
Organic Cation Transporter 2 (OCT2) substrates
Prevention or Management | Avoid concomitant use with OCT2 substrates while taking ROMVIMZA. Refer to the Prescribing Information of the OCT2 substrate for dose modifications if concomitant use cannot be avoided.
Mechanism and Clinical Effect(s) | This recommendation is based upon a mechanistic understanding of vimseltinib pharmacokinetics and it being an OCT2 inhibitor in vitro [see Clinical Pharmacology (12.3)]. Concomitant use of ROMVIMZA with OCT2 substrates may increase exposure of these substrates; however, this has not been studied clinically.

8 USE IN SPECIFIC POPULATIONS

8.1 Pregnancy

Risk Summary

Based on data from animal studies and its mechanism of action, ROMVIMZA can cause fetal harm when administered to a pregnant woman. There are no available data on vimseltinib use in pregnant women to evaluate for a drug-associated risk of major birth defects, miscarriage, or adverse maternal or fetal outcomes. In female rats administered vimseltinib during the period of organogenesis, fetal structural abnormalities occurred at exposures that were at least 3 times the recommended dose based on AUC (see Data). Advise pregnant women of the potential risk to a fetus.

The background risk of major birth defects and miscarriage for the indicated population is unknown. All pregnancies have a background risk of birth defect, loss, or other adverse outcomes. In the U.S. general population, the estimated background risk of major birth defects and miscarriage in clinically recognized pregnancies is 2 to 4% and 15 to 20%, respectively.

Data

Animal Data

In a rat embryo-fetal development study, pregnant female rats were dosed once daily during the period of organogenesis (gestational days 6 to 17) at doses of 2.5, 5, or 15 mg/kg/day. Structural abnormalities (skeletal variations) occurred at ≥2.5 mg/kg/day (approximately 3 times the exposure at the recommended dose based on AUC). Additional structural abnormalities (cardiac malformations) were observed at the highest dose of 15 mg/kg/day (approximately 23 times the exposure at the recommended dose based on AUC).

8.2 Lactation

Risk Summary

There are no data on the presence of vimseltinib or its metabolites in either human or animal milk or its effects on a breastfed child or on milk production. Because of the potential for serious adverse reactions in the breastfed child, advise women not to breastfeed during treatment with ROMVIMZA and for 1 month after the last dose.

8.3 Females and Males of Reproductive Potential

ROMVIMZA can cause fetal harm when administered to a pregnant woman [see Use in Specific Populations (8.1)].

Pregnancy Testing

Verify pregnancy status in females of reproductive potential prior to the initiation of ROMVIMZA [see Use in Specific Populations (8.1)].

Contraception

Females

Advise females of reproductive potential to use effective contraception during treatment with ROMVIMZA and for 1 month after the last dose [see Warnings and Precautions (5.2), Nonclinical Toxicology (13.1)].

Males

Advise males that are partnered with females of reproductive potential to use effective contraception during treatment with ROMVIMZA and for 1 month after the last dose [see Warnings and Precautions (5.2), Nonclinical Toxicology (13.1)].

Infertility

Females and Males

Based on findings from animal studies, ROMVIMZA may impair fertility [see Nonclinical Toxicology (13.1)].

8.4 Pediatric Use

The safety and effectiveness of ROMVIMZA in pediatric patients have not been established.

Animal Toxicity Data

In a 26-week repeat-dose toxicology study, rats administered vimseltinib at ≥2.5 mg/kg/day had physeal thickening and decay of the incisors and molars. Bone and tooth toxicities occurred at exposures at least 8 times the recommended dose based on AUC.

8.5 Geriatric Use

Clinical studies of ROMVIMZA did not include a sufficient number of patients aged 65 years and older to determine whether they respond differently from younger patients.

8.6 Hepatic Impairment

No dose adjustment is recommended for patients with mild (bilirubin ≤upper limit of normal (ULN) and aspartate aminotransferase (AST) >ULN or bilirubin >1x to 1.5x ULN and any AST) hepatic impairment. ROMVIMZA has not been studied in patients with moderate (bilirubin >1.5x to 3x ULN and any AST) or severe (bilirubin >3x ULN and any AST) hepatic impairment [see Clinical Pharmacology (12.3)].

11 DESCRIPTION

Vimseltinib is a kinase inhibitor. The chemical name of vimseltinib dihydrate is 3-methyl-5-[6-methyl-5-[2-(1-methylpyrazol-4-yl)pyridin-4-yl]oxypyridin-2-yl]-2-(propan-2-ylamino)pyrimidin-4-one, dihydrate.

Vimseltinib is a white to off-white crystalline solid. Vimseltinib is a weak base, very slightly soluble in water. The molecular formula for vimseltinib dihydrate is C23H25N7O2 • 2 H2O, and the molecular weight is 467.52 g/mol. The chemical structure is:

ROMVIMZA (vimseltinib) capsules are supplied as printed hard gelatin capsules containing 14 mg, 20 mg, or 30 mg of vimseltinib (equivalent to 15.18 mg, 21.68 mg, or 32.52 mg of vimseltinib dihydrate, respectively). The capsule contains the following inactive ingredients: crospovidone, lactose monohydrate, and magnesium stearate. The capsule shell contains Brilliant Blue FCF (30 mg strength), erythrosine (30 mg strength), gelatin, Sunset Yellow FCF (14 mg and 20 mg strengths), tartrazine (20 mg), and titanium dioxide.

12 CLINICAL PHARMACOLOGY

12.1 Mechanism of Action

Vimseltinib is a kinase inhibitor that inhibits colony-stimulating factor 1 receptor (CSF1R). In vitro, vimseltinib inhibited CSF1R autophosphorylation, signaling induced by CSF1 ligand binding, and proliferation of cells expressing CSF1R.

12.2 Pharmacodynamics

Exposure-Response Relationship

Higher vimseltinib exposure is associated with an increased risk of all grades of edema, rash, increased AST, and increased ALT.

Vimseltinib exposure-response relationship for efficacy and time course of pharmacodynamic response have not been fully characterized.

Cardiac Electrophysiology

At the maximum recommended dose of ROMVIMZA, clinically significant QTc interval prolongation was not observed. However, the largest mean increase in QTc interval was 8.2 ms (upper confidence internal = 12.3 ms) after administration of vimseltinib 40 mg once daily for 5 days (3.3 times the maximum recommended weekly dose). The increase in QTc interval was concentration-dependent [see Clinical Pharmacology (12.3)].

12.3 Pharmacokinetics

Vimseltinib pharmacokinetic parameters were determined following a single oral dose of 30 mg or at steady state following multiple doses of 30 mg twice weekly and are provided as mean (CV%) unless otherwise specified.

Vimseltinib peak plasma concentration (Cmax) is 283 ng/mL (36%) or 747 ng/mL (39%) after a single dose or at steady state, respectively, and area under the time concentration curve (AUC0-inf) is 46,900 ng•h/mL (45%) after a single dose and AUC0-24hr is 13,400 ng•h/mL (45%) at steady state.

Vimseltinib pharmacokinetics are dose-proportional.

Absorption

Vimseltinib median time to Cmax (Tmax) is 1 hour (0.5 to 4 hours).

Effect of Food

No clinically significant differences in vimseltinib pharmacokinetics were observed following administration of a high-fat meal (800 to 1000 kcal, 50% fat), compared to fasted conditions.

Distribution

Vimseltinib volume of distribution (V/F) is 90 L (16%). Vimseltinib is 96.5% bound to human plasma proteins.

Elimination

Vimseltinib elimination half-life (t1/2) is approximately 6 days (32%) with a clearance (CL/F) of 0.5 L/h (23%).

Metabolism

Vimseltinib is primarily metabolized by oxidation, N-demethylation, and N-dealkylation; secondary biotransformation pathways included N-demethylation, dehydrogenation, and oxidation. CYP450 enzymes are not anticipated to play a major role in the metabolism of vimseltinib.

Excretion

Approximately 43% of the dose was recovered in feces (9.1% unchanged) and 38% in urine (5.1% unchanged) after a single radiolabeled dose.

Specific Populations

No clinically significant differences in the pharmacokinetics of vimseltinib were observed based on age (20 to 91 years), sex, race (Asian, Black or African American, White), body weight (43 to 150 kg), tumor (TGCT or other malignant solid tumors), and mild to moderate renal impairment (estimated glomerular filtration rate [eGFR] ≥30 mL/min calculated by CKD-EPI equation). The effect of severe renal impairment (eGFR <30 mL/min) or moderate to severe hepatic impairment (total bilirubin >1.5 x ULN with any AST) on vimseltinib pharmacokinetics is unknown.

Drug Interaction Studies

Clinical Studies and Model-Informed Approaches

P-glycoprotein (P-gp) inhibitors: Dabigatran (a P-gp substrate) AUC0-inf and Cmax are predicted to increase 2- to 3-fold with concomitant use with vimseltinib 30 mg twice weekly.

Dabigatran Cmax and AUC0-inf are predicted to increase up to 1.3-fold if administered 4 hours after administration of vimseltinib 30 mg twice weekly.

Other Drugs: No clinically significant differences in vimseltinib pharmacokinetics were observed when used concomitantly with itraconazole (a P-gp inhibitor) or rabeprazole (a proton pump inhibitor).

In Vitro Studies

CYP 450 enzymes: Vimseltinib is not a substrate of CYP1A2, CYP2B6, CYP2C8, CYP2C9, CYP2C19, CYP2D6, and CYP3A.

Vimseltinib is not an inhibitor of CYP1A2, CYP2B6, CYP2C8, CYP2C9, CYP2C19, CYP2D6, and CYP3A4.

Vimseltinib is not an inducer of CYP1A2, CYP2B6, or CYP3A4.

Transporter systems: Vimseltinib is a P-gp substrate but is not a substrate of BCRP, BSEP, OATP1B1, OATP1B3, OAT1, OAT3, OCT2, MATE1, and MATE2-K.

Vimseltinib inhibits P-gp, BCRP, BSEP, OATP1B1, OATP1B3, OCT2, BSEP, MATE1, and MATE2-K. Vimseltinib does not inhibit OAT1 and OAT3. Vimseltinib may increase serum creatinine by decreasing renal tubular secretion of creatinine; this may occur due to inhibition of renal transporters OCT2 and MATE1 and may not affect renal function.

13 NONCLINICAL TOXICOLOGY

13.1 Carcinogenesis, Mutagenesis, Impairment of Fertility

In a 6-month transgenic mouse carcinogenicity study at doses up to 12.5 mg/kg/day, vimseltinib was negative for carcinogenic findings.

In a 2-year rat carcinogenicity study, female rats were orally administered vimseltinib at doses of 0.15, 0.45, or 1.5 mg/kg/day. There was no evidence of vimseltinib-related neoplasms in female rats. Male rats were orally administered vimseltinib at doses of 0.1, 0.3, or 1.0 mg/kg/day. There was a statistically significant increase in the combined incidence of benign and malignant pheochromocytomas in the adrenal gland of male rats administered 1.0 mg/kg/day (approximately 1.4 times the exposure at the recommended dose based on AUC). The relevance of this finding to human carcinogenic risk is not known. In male rats receiving 1.0 mg/kg/day, two out of sixty rats were identified as having sarcomas in the synovium of the femorotibial joint. The sarcoma finding was not statistically significant and its relevance to human carcinogenic risk is not known.

Vimseltinib was not mutagenic in the bacterial reverse mutation assay (Ames). In an in vitro micronucleus assay, vimseltinib increased micronuclei after a 24 -hour incubation in the absence of metabolic activation. In vivo, vimseltinib administered to rats at doses up to 200 mg/kg/day did not increase bone marrow micronucleated polychromatic erythrocytes, nor did vimseltinib increase liver DNA strand breaks.

In a fertility and early embryonic development study, male rats were administered 1, 2.5, or 5 mg/kg/day of vimseltinib starting 10 weeks before cohabitation, during cohabitation with untreated females, and at least 2 weeks post-cohabitation. Lower epididymal and testes weights were observed at 5 mg/kg/day (approximately 12 times the exposure at the recommended dose based on AUC). There were no treatment-related effects on mating, fertility, or sperm parameters at any dose tested. Female rats were administered 2.5, 5, or 10 mg/kg/day of vimseltinib 2 weeks prior to cohabitation with untreated males and during cohabitation until gestational day 7. Although there were no treatment-related effects on mating or estrous cycles, vimseltinib administered daily resulted in post-implantation loss at 10 mg/kg/day in female rats (approximately 20 times the exposure at the recommended dose based on AUC).

In a 26-week repeat-dose general toxicology study, recovery male rats that were administered 2.5 or 5 mg/kg/day had moderate to marked reductions in sperm and marked testicular atrophy (1 of 5 and 2 of 5 animals, respectively) corresponding to approximately 6 and 12 times the exposure at the recommended dose based on AUC, respectively. In a 39-week repeat-dose general toxicology study, minimal to moderate epididymal mineralization occurred in male dogs administered ≥4 mg/kg/day corresponding to exposures lower than the exposure at the recommended dose based on AUC.

13.2 Animal Toxicology and/or Pharmacology

In a 26-week repeat-dose general toxicology study in rats, chronic progressive nephropathy occurred at vimseltinib doses of ≥2.5 mg/kg/day (approximately 6 times the exposure at the recommended dose based on AUC). Degeneration of blood vessels (perivascular inflammation and necrosis of arteries and arteriole walls) occurred in multiple tissues at 5 mg/kg/day (approximately 12 times the exposure at the recommended dose based on AUC).

In a 39-week repeat-dose general toxicology study in dogs, skin depigmentation in the head and legs occurred at vimseltinib doses of ≥4 mg/kg/day corresponding to exposures lower than the exposure at the recommended dose based on AUC.

In a 2-year rat carcinogenicity study, synovial hyperplasia and inflammation occurred in the femorotibial joint at vimseltinib doses of ≥0.3 mg/kg/day corresponding to exposures lower than the exposure at the recommended dose based on AUC.

14 CLINICAL STUDIES

The efficacy of ROMVIMZA was evaluated in MOTION (NCT05059262), a phase 3, double-blind, multicenter, randomized (2:1), placebo-controlled study in patients with TGCT for whom surgical resection may cause worsening functional limitation or severe morbidity. Eligible patients had a confirmed diagnosis of TGCT with measurable disease per the Response Evaluation Criteria in Solid Tumors (RECIST v1.1) with at least one lesion having a minimum size of 2 cm. Patients were randomized to placebo or ROMVIMZA 30 mg twice weekly for 24 weeks. Randomization was stratified by tumor location (lower limb versus all other) and region (United States [US] versus non-US). At Week 25, patients who completed the double-blind, randomized part of the trial were eligible to advance to an ongoing, open-label extension study in which all patients received ROMVIMZA.

The major efficacy outcome measure was overall response rate (ORR) as assessed by blinded independent radiological review (IRR) per RECIST v1.1 at Week 25. Additional efficacy outcomes measured at Week 25 included ORR as assessed using tumor volume score (TVS), mean change from baseline in active range of motion of the affected joint at Week 25 measured by goniometry assessments, change from baseline in the Patient-Reported Outcomes Measurement Information System-Physical Function (PROMIS-PF) 15-item score (upper and lower extremity items), and response of at least a 30% improvement in the mean Brief Pain Inventory (BPI) Worst Pain numeric rating scale (NRS) score without a 30% or greater increase in narcotic analgesic use.

A total of 123 patients were randomized: 83 to ROMVIMZA and 40 to placebo during the double-blind period of the study. The median age was 44 years (range 20 to 78 years); 59% of patients were female; 65% were White, 4% were Asian, 3% were Black or African American, and 28% were not reported or unknown; 69% were not Hispanic or Latino, 3% were Hispanic or Latino, and 28% were not reported or unknown; 74% of patients had prior surgery; 69% of patients had diffuse TGCT; and 23% of patients were previously treated with systemic therapy. Disease locations were knee (67%), ankle (12%), hip (10%), other (5%), foot (3.3%), and wrist (2.4%).

A statistically significant improvement in ORR was demonstrated in patients randomized to ROMVIMZA compared with placebo. Efficacy results in MOTION are summarized in Table 6.

Table 6: Efficacy Results Assessed at Week 25 for MOTION
Efficacy Parameter | ROMVIMZA N = 83 | Placebo N = 40
Overall Response Rate per RECIST v1.1 (95% CI) | 40% (29%, 51%) | 0% (0%, 9%)
Complete Response | 5% | 0%
Partial Response | 35% | 0%
p-value | <0.0001
Duration of Response^1
Median (Range in months)^2 | NR (2.5+, 19.4+) | N/A
DOR ≥6 months | 28 (85%) | -
DOR ≥9 months | 19 (58%) | -
Active ROM^3
Patients with data at baseline and Week 25, n | 73 | 33
Baseline mean (SD) | 63.0 (29.4) | 62.9 (32.2)
Mean change from baseline^4 (95% CI) | 18.4 (5.6, 31.2) | 3.8 (-10.5, 18.0)
Difference in LS means (95% CI) | 14.6% (4.0, 25.3)
p-value | 0.0077
PROMIS-PF (15-Item score; ranges from 0-100)^5
Patients with data at baseline and Week 25, n | 63 | 30
Baseline mean (SD) | 39.0 (6.1) | 38.5 (6.0)
Mean change from baseline^4 (95% CI) | 4.6 (2.7, 6.5) | 1.3 (-0.5, 3.0)
Difference in LS means (95% CI) | 3.3 (1.4, 5.2)
p-value | 0.0007
BPI-30 Response^6
Patients with data at baseline and Week 25, n | 68 | 31
Responders, n (%) | 40 (48.2%) | 9 (22.5%)
(95% CI) | (37.1%, 59.4%) | (10.8%, 38.5%)
Difference in responder rate (95% CI)^7 | 26.2% (9.5, 42.8)
p-value | 0.0056
NR=Not reached; N/A=Not applicable; AMA=American Medical Association; BPI=Brief Pain Inventory; CI=confidence interval; LS=least squares; MMRM=mixed model for repeated measures; n=number of patients in the category; N=sample size; PROMIS-PF=Patient-reported Outcomes Measurement Information System-Physical Function; ROM=range of motion; SD= Standard deviation.
^1 DOR results are based on an additional 6 months of follow-up from the time of ORR analysis.
^2 The median DOR was estimated using the Kaplan-Meier method. “+” indicates that the patient's response was ongoing at last assessment as of the data cutoff date.
^3 Active ROM was normalized to the AMA reference standard.
^4 Mean change from baseline was estimated from the MMRM for each corresponding endpoint. Baseline means presented include all patients and not only the ones with data at baseline and Week 25.
^5 Data for PROMIS-PF is largely based on lower limb extremity assessment due to tumor location as described above. Higher scores of PROMIS-PF indicate better physical functioning.
^6 BPI response in Worst Pain is defined as at least a 30% improvement in the mean BPI Worst Pain NRS score (0-10 NRS) without a 30% or greater increase in narcotic analgesic use at Week 25.
^7 95% CI for the difference in response rates based on the stratified Mantel-Haenszel method.

ORR by TVS was 67% (95% CI: 56, 77) in patients randomized to ROMVIMZA and 0% in patients randomized to placebo; p-value <0.0001.

Individual patient results of change from baseline in active ROM at Week 25 (ROMVIMZA N = 73; placebo N=33) are shown in Figure 1.

Figure 1: Change from Baseline in Active Range of Motion at Week 25 for MOTION

* Percent normal reference range for the affected joint.

^+ Response by RECIST v1.1.

16 HOW SUPPLIED/STORAGE AND HANDLING

Table 7: ROMVIMZA 14 mg, 20 mg, and 30 mg Capsules
Strength | Description | Package Size and Type | NDC Number
14 mg | Size 4 hard gelatin capsule with white body and orange cap with black print “DCV14”, packed in oPA-film/ aluminum foil /PVC-film blisters with push-through aluminum foil lidding. | Each carton contains one child-resistant blister pack containing 8 capsules (four-week supply) | 73207-302-40
20 mg | Size 2 hard gelatin capsule with white body and yellow cap with black print “DCV20”, packed in oPA-film/ aluminum foil /PVC-film blisters with push-through aluminum foil lidding. | Each carton contains one child-resistant blister pack containing 8 capsules (four-week supply) | 73207-303-40
30 mg | Size 1 hard gelatin capsule with white body and light blue cap with black print “DCV30”, packed in oPA-film/ aluminum foil /PVC-film blisters with push-through aluminum foil lidding. | Each carton contains one child-resistant blister pack containing 8 capsules (four-week supply) | 73207-304-40

Store at controlled room temperature 20°C to 25°C (68°F to 77°F); excursions permitted to 15°C to 30°C (59°F to 86°F) [See USP Controlled Room Temperature].

Store capsules in their original blister packs until ready to be taken. Do not store ROMVIMZA in another container.

17 PATIENT COUNSELING INFORMATION

Advise the patient to read the FDA approved patient labeling (Medication Guide).

Hepatotoxicity

Advise patients there may be a potential risk of hepatotoxicity and that they will need to undergo laboratory tests to monitor liver function and to immediately report any signs or symptoms of severe liver injury to their healthcare provider [see Warnings and Precautions (5.1)].

Embryo-Fetal Toxicity

- Advise pregnant women and females of reproductive potential of the potential risk to the fetus. Advise females of reproductive potential to inform their healthcare provider of a known or suspected pregnancy [see Warnings and Precautions (5.2), Use in Specific Populations (8.1, 8.3)].
- Advise females of reproductive potential to avoid pregnancy and to use effective contraception during treatment with ROMVIMZA and for 1 month after the last dose [see Warnings and Precautions (5.2), Use in Specific Populations (8.1, 8.3)].
- Advise males with female partners of reproductive potential to use effective contraception during treatment and for 1 month after the last dose of ROMVIMZA [see Warnings and Precautions (5.2) and Use in Specific Populations (8.3)].

Lactation

Advise females not to breastfeed during treatment with ROMVIMZA and for 1 month after the final dose [see Use in Specific Populations (8.2)].

Infertility

Advise patients that ROMVIMZA may impair fertility [see Use in Specific Populations (8.3), Nonclinical Toxicology (13.1)].

Allergic Reactions to FD&C Yellow No. 5 (Tartrazine) and No. 6 (Sunset Yellow FCF)

Advise patients that ROMVIMZA 20 mg contains FD&C Yellow No. 5 (tartrazine), which may cause allergic-type reactions (including bronchial asthma) in certain susceptible persons or in patients who also have aspirin hypersensitivity [see Warnings and Precautions (5.3)]. Advise patients ROMVIMZA 14 mg and ROMVIMZA 20 mg contains FD&C Yellow No. 6 (Sunset Yellow FCF) which may cause allergic-type reactions [see Warnings and Precautions (5.3)].

Administration

- Instruct patients that doses should be taken twice weekly at least 72 hours apart [see Dosage and Administration (2.1)].
- Instruct patients to swallow capsules whole (do not open, break, or chew) [see Dosage and Administration (2.1)].

Drug Interactions

Advise patients to inform their healthcare providers of all concomitant products, including over-the-counter products and supplements [see Dosage and Administration (2.3), Drug Interactions (7.1)].

Manufactured for and marketed by:

Deciphera Pharmaceuticals, LLC

200 Smith Street, Waltham, MA 02451

MEDICATION GUIDE
ROMVIMZATM (rom-vim-zah)
(vimseltinib)
capsules

What is the most important information I should know about ROMVIMZA?
ROMVIMZA can cause serious side effects, including:
Liver problems. Increased liver enzymes in your blood are common with ROMVIMZA.
Your healthcare provider will do blood tests to check for liver problems:

- before starting treatment with ROMVIMZA,
- 2 times each month for the first 2 months of treatment,
- then 1 time every 3 months for the first year of treatment and as clinically indicated thereafter.

If you develop liver problems during treatment with ROMVIMZA, your healthcare provider may temporarily stop treatment, decrease your dose, or permanently stop treatment depending on how severe your liver problems are.
Tell your healthcare provider right away if you develop any signs or symptoms of liver problems during treatment with ROMVIMZA including:

- yellowing of your skin or the white part of your eyes
- dark urine
- lack or loss of appetite
- right upper stomach-area (abdomen) pain or tenderness
- feeling overly tired

- nausea
- vomiting
- fever
- rash
- itching

See “What are the possible side effects of ROMVIMZA?” for more information about side effects.

What is ROMVIMZA?
ROMVIMZA is a prescription medicine used to treat adults with symptomatic tenosynovial giant cell tumor (TGCT) when surgery may make the symptoms worse or cause severe problems.
It is not known if ROMVIMZA is safe and effective in children.

Before taking ROMVIMZA, tell your healthcare provider about all of your medical conditions, including if you:

- have or had liver problems
- are pregnant or plan to become pregnant. ROMVIMZA can harm your unborn baby.
  Females who are able to become pregnant:
  - Your healthcare provider will do a pregnancy test before you start treatment with ROMVIMZA.
  - Use effective birth control (contraception) during treatment with ROMVIMZA and for 1 month after the last dose. Talk to your healthcare provider about birth control methods that may be right for you.
  - Tell your healthcare provider right away if you become pregnant or you think you may be pregnant during treatment with ROMVIMZA.
  Males with female partners who are able to become pregnant:
  - Use effective birth control (contraception) during treatment with ROMVIMZA and for 1 month after the last dose.
  - Tell your healthcare provider right away if your female partner becomes pregnant or thinks she may be pregnant during treatment with ROMVIMZA.
- are breastfeeding or plan to breastfeed. It is not known if ROMVIMZA passes into your breast milk. Do not breastfeed during treatment with ROMVIMZA and for 1 month after the last dose.

Tell your healthcare provider about all the medicines you take, including prescription and over-the-counter medicines, vitamins, and herbal supplements.
Taking ROMVIMZA with certain other medicines may affect the way that ROMVIMZA or the other medicine works and may increase your risk of side effects. Know the medicines you take. Keep a list of them to show to your healthcare provider and pharmacist when you get a new medicine.

How should I take ROMVIMZA?

- Take ROMVIMZA exactly as your healthcare provider tells you to.
- Do not change your dose or stop taking ROMVIMZA unless your healthcare provider tells you to.
- Take ROMVIMZA 2 times a week with at least 72 hours between doses. Follow the dosing directions and schedule on your blister package and take ROMVIMZA on the same days each week.
- Take ROMVIMZA with or without food.
- Swallow ROMVIMZA capsules whole. Do not open, break, or chew the capsules.
- If you miss a dose of ROMVIMZA by 48 hours or less, take the missed dose as soon as possible and take the next dose on its regularly scheduled day. If you miss your dose by more than 48 hours, skip the missed dose, and take the next dose on its regularly scheduled day.
- If you vomit within 30 minutes of taking a dose of ROMVIMZA, take another dose. If you vomit more than 30 minutes after taking your dose, do not take another dose and take the next dose on its regularly scheduled day.
- If you take more than the prescribed dose of ROMVIMZA, call your healthcare provider.

What are the possible side effects of ROMVIMZA?
ROMVIMZA can cause serious side effects.

- See “What is the most important information I should know about ROMVIMZA?”
- Allergic reactions to FD&C Yellow No. 5 and FD&C Yellow No. 6. ROMVIMZA 20 mg capsules contain the inactive ingredients FD&C Yellow No. 5 (tartrazine) and FD&C Yellow No. 6 (Sunset Yellow FCF). ROMVIMZA 14 mg capsules contain the inactive ingredient FD&C Yellow No. 6 (Sunset Yellow FCF). FD&C Yellow No. 5 (tartrazine) can cause allergic-type reactions (including bronchial asthma) in certain people, especially people who also have an allergy to aspirin. FD&C Yellow No. 6 (Sunset Yellow FCF) can also cause allergic reactions. Tell your healthcare provider if you get hives, rash, or trouble breathing during treatment with ROMVIMZA.

The most common side effects of ROMVIMZA include:

- swelling around your eyes
- tiredness
- rash
- increased cholesterol levels in your blood

- swelling of your hands or feet
- swelling of your face
- decreased white blood cells
- itchy skin

ROMVIMZA may cause fertility problems, which may affect your ability to have children. Talk to your healthcare provider if you have concerns about fertility.
These are not all the possible side effects of ROMVIMZA. Call your doctor for medical advice about side effects. You may report side effects to FDA at 1-800-FDA-1088.

How should I store ROMVIMZA?

- Store ROMVIMZA capsules at room temperature between 68ºF to 77ºF (20ºC to 25ºC).
- Store ROMVIMZA capsules in the original blister pack until you are ready to take them. Do not store ROMVIMZA capsules in another container.
- The blister packs are child resistant.

Keep ROMVIMZA and all medicines out of the reach of children.

General information about the safe and effective use of ROMVIMZA.
Medicines are sometimes prescribed for purposes other than those listed in a Medication Guide. Do not use ROMVIMZA for a condition for which it was not prescribed. Do not give ROMVIMZA to other people, even if they have the same symptoms that you have. It may harm them. You can ask your pharmacist or healthcare provider for information about ROMVIMZA that is written for health professionals.

What are the ingredients in ROMVIMZA?
Active ingredient: vimseltinib
Inactive ingredients: crospovidone, lactose monohydrate, and magnesium stearate
The capsule shells contain:
14 mg capsule: Sunset Yellow FCF, gelatin, and titanium dioxide
20 mg capsule: Sunset Yellow FCF, tartrazine, gelatin, and titanium dioxide
30 mg capsule: Brilliant Blue FCF, erythrosine, gelatin, and titanium dioxide
The ink contains black iron oxide, potassium hydroxide, propylene glycol, shellac and strong ammonia solution.
Manufactured for and marketed by: Deciphera Pharmaceuticals, LLC, 200 Smith Street, Waltham, MA 02451
ROMVIMZA is a trademark of Deciphera, LLC.
For more information, call 1-888-724-3274 or go to www.ROMVIMZA.com

This Medication Guide has been approved by the U.S. Food and Drug Administration.

Issued: 02/2025

Principal Display Panel – 14 mg Carton Label

NDC 73207-302-40

Rx only

14 mg
per capsule

Romvimza™
(vimseltinib) capsules

8 capsules (4-week supply)

Contains one blister pack

Principal Display Panel – 20 mg Carton Label

NDC 73207-303-40

Rx only

20 mg
per capsule

Romvimza™
(vimseltinib) capsules

8 capsules (4-week supply)

Contains one blister pack

Principal Display Panel – 30 mg Carton Label

NDC 73207-304-40

Rx only

30 mg
per capsule

Romvimza™
(vimseltinib) capsules

8 capsules (4-week supply)

Contains one blister pack